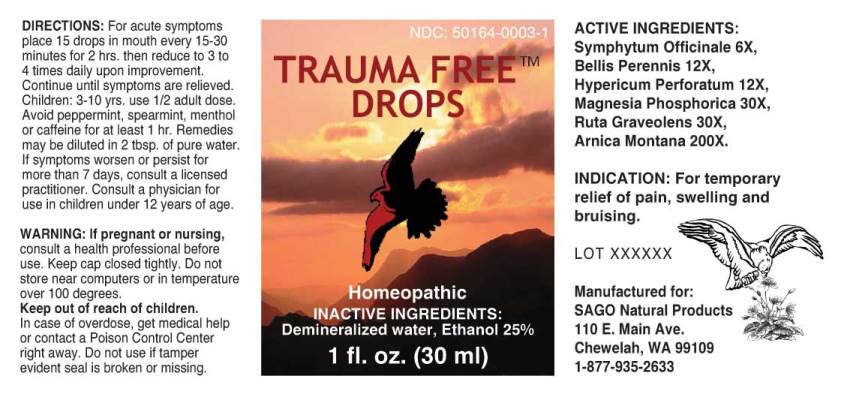 DRUG LABEL: Trauma Free
NDC: 50164-0004 | Form: LIQUID
Manufacturer: Sago Natural Products
Category: homeopathic | Type: HUMAN OTC DRUG LABEL
Date: 20160624

ACTIVE INGREDIENTS: COMFREY ROOT 6 [hp_X]/1 mL; BELLIS PERENNIS 12 [hp_X]/1 mL; HYPERICUM PERFORATUM 12 [hp_X]/1 mL; MAGNESIUM PHOSPHATE, DIBASIC TRIHYDRATE 30 [hp_X]/1 mL; RUTA GRAVEOLENS FLOWERING TOP 30 [hp_X]/1 mL; ARNICA MONTANA 200 [hp_X]/1 mL
INACTIVE INGREDIENTS: WATER; ALCOHOL

Drug Facts:

ACTIVE INGREDIENTS:

Symphytum Officinale 6X, Bellis Perennis 12X, Hypericum Perforatum 12X, Magnesia Phosphorica 30X, Ruta Graveolens 30X, Arnica Montana 200X.

INDICATIONS:

For temporary relief of pain, swelling and bruising.

WARNINGS:

If pregnant or nursing, consult a health professional before use.

Keep cap closed tightly.

Do not store near computers or in temperature over 100 degrees.

Keep out of reach of children. In case of overdose, get medical help or contact a Poison Control Center right away.

Do not use if tamper evident seal is broken or missing.

Keep out of reach of children. In case of overdose, get medical help or contact a Poison Control Center right away.

DIRECTIONS:

For acute symptoms place 15 drops in mouth every 15-30 minutes for 2 hrs. then reduce to 3 to 4 times daily upon improvement. Continue until symptoms are relieved. Children: 3-10 yrs. use 1/2 adult dose. Avoid peppermint, spearmint, menthol or caffeine for at least 1 hr. Remedies may be diluted in 2 tbsp. of pure water. If symptoms worsen or persist for more than 7 days, consult a licensed practitioner. Consult a physician for use in children under 12 years of age.

INDICATIONS:

For temporary relief of pain, swelling and bruising.

INACTIVE INGREDIENTS:

Demineralized water, Ethanol 25%.

QUESTIONS:

Manufactured for:

SAGO Natural Products

110 E. Main Ave.

Chewelah, WA 99109

PACKAGE LABEL DISPLAY:

NDC 50164-0004-1

TRAUMA FREE
DROPS

Homeopathic

2 fl. oz. (60 ml)